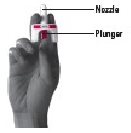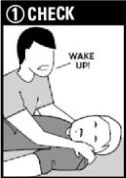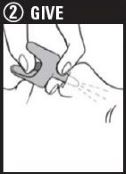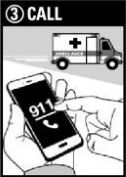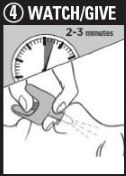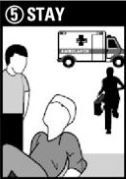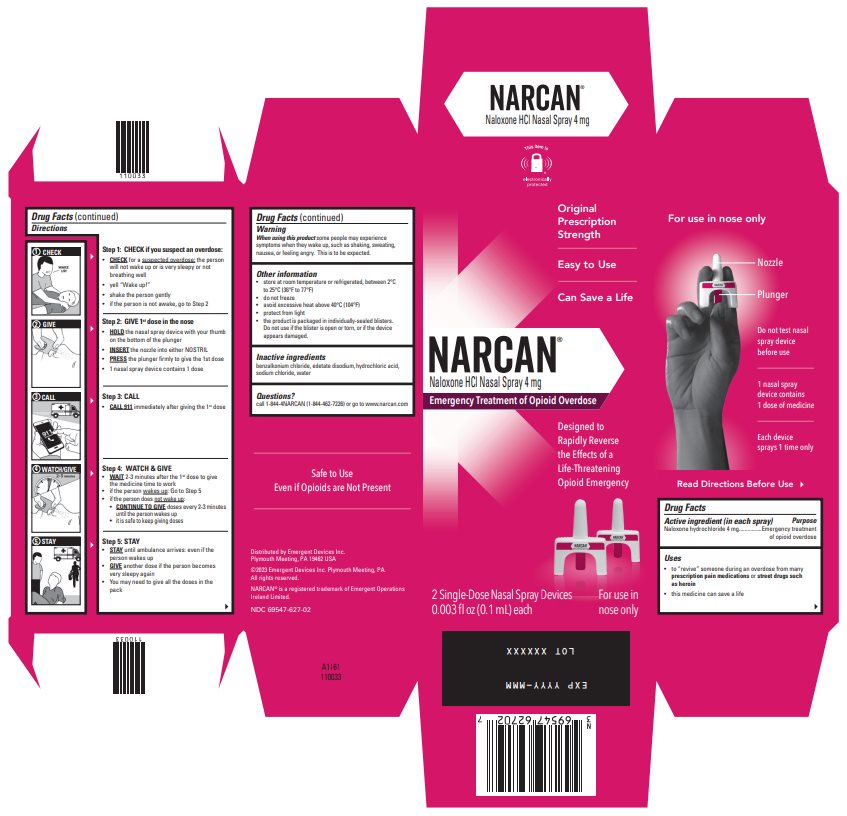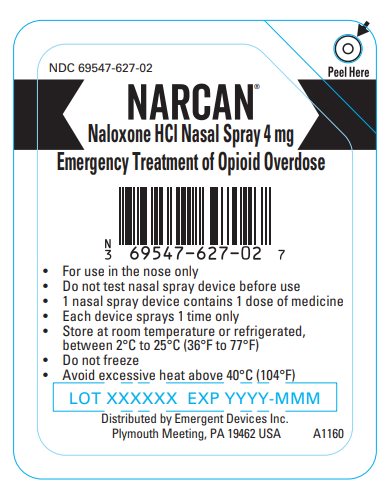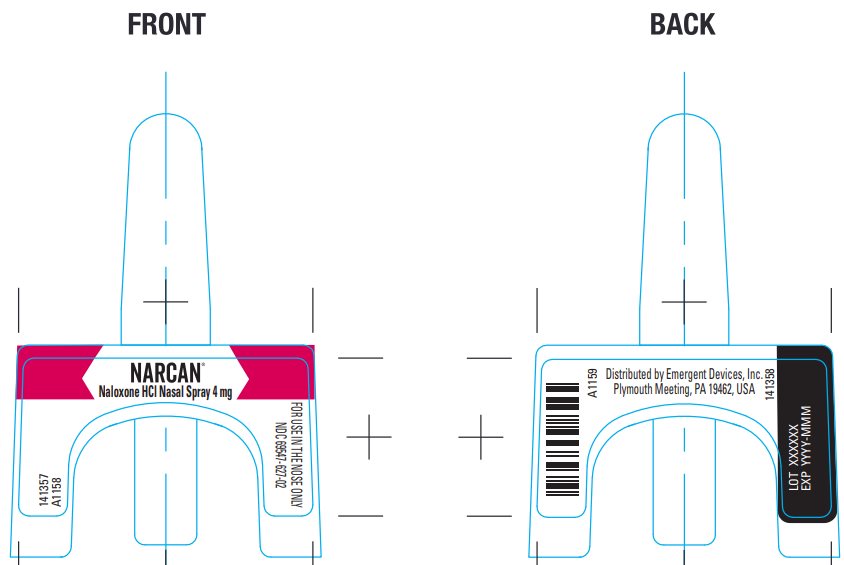 DRUG LABEL: NARCAN
NDC: 69547-627 | Form: SPRAY
Manufacturer: Emergent Devices Inc.
Category: otc | Type: HUMAN OTC DRUG LABEL
Date: 20230808

ACTIVE INGREDIENTS: NALOXONE HYDROCHLORIDE 4 mg/0.1 mL
INACTIVE INGREDIENTS: BENZALKONIUM CHLORIDE; EDETATE DISODIUM; SODIUM CHLORIDE; WATER; HYDROCHLORIC ACID

NARCAN® Naloxone HCl Nasal Spray 4 mg Drug Facts

Active ingredient (in each spray)

Naloxone Hydrochloride 4 mg

Purpose

Emergency treatment of opioid overdose

Uses

- to “revive” someone during an overdose from many prescription pain medications or street drugs such as heroin
- this medicine can save a life

Warning

- When using this product some people may experience symptoms when they wake up, such as, shaking, sweating, nausea, or feeling angry. This is to be expected.

Directions

NARCAN®
Naloxone HCl Nasal Spray 4 mg

Emergency Treatment of Opioid Overdose

Important:

- For use in the nose only
- Do not test nasal spray device before use
- 1 nasal spray device contains 1 dose of medicine
- Each device sprays 1 time only

Step 1: CHECK if you suspect an overdose:

- CHECK for a suspected overdose: the person will not wake up or is very sleepy or not breathing well
  - yell “Wake up!”
  - shake the person gently
  - if the person is not awake, go to Step 2

Step 2: Give 1st dose in the nose

- HOLD the nasal spray device with your thumb on the bottom of the plunger
- INSERT the nozzle into either NOSTRIL
- PRESS the plunger firmly to give the 1st dose
- 1 nasal spray device contains 1 dose

Step 3: CALL 911

- CALL 911 immediately after giving the lst dose

Step 4: WATCH & GIVE

- WAIT 2-3 minutes after the lst dose to give the medicine time to work
- if the person wakes up: Go to Step 5
- if the person does not wake up:
  - CONTINUE TO GIVE doses every 2-3 minutes until the person wakes up
  - it is safe to keep giving doses

Step 5: STAY

- STAY until ambulance arrives: even if the person wakes up
- GIVE another dose if the person becomes very sleepy again
- You may need to give all the doses in the pack

For opioid emergencies, call 911. For questions on NARCAN, call 1-844-4NARCAN (1-844-462-7226) or go to www.narcan.com.

©2023 Emergent Devices Inc. EMERGENT® and NARCAN® are registered trademarks of Emergent BioSolutions Inc, or its subsidiaries.

Other Information

- store at room temperature or refrigerated, between 2°C to 25°C (36°F to 77°F)
- do not freeze
- avoid excessive heat above 40°C (104°F)
- protect from light
- the product is packaged in individually-sealed blisters.
  Do not use if the blister is open or torn, or if the device appears damaged.

Inactive Ingredients

benzalkonium chloride, edetate disodium, hydrochloric acid, sodium chloride, water

Questions?

Call 1-844-4NARCAN (1-844-462-7226) or go to www.narcan.com

Package/Label Principal Display Panel – Carton Label

NARCAN®
Naloxone HCl Nasal Spray 4 mg
Emergency Treatment of Opioid Overdose

Original
Prescription
Strength

Easy to Use

Can Save a Life

Designed to
Rapidly Reverse
the Effects of a
Life-Threatening
Opioid Emergency

2 Single-Dose Nasal Spray Devices
0.003 fl oz (0.1 mL) each

For use in
nose only

Distributed by Emergent Devices Inc.
Plymouth Meeting, PA 19462 USA

©2023 Emergent Devices Inc. Plymouth Meeting, PA.
All rights reserved.

NARCAN® is a registered trademark of Emergent Operations
Ireland Limited.

NDC 69547-627-02

Package/Label Principal Display Panel - 4 mg Vial Package

NDC 69547-627-02

NARCAN®
Naloxone HCl Nasal Spray 4 mg
Emergency Treatment of Opioid Overdose

- For use in the nose only
- Do not test nasal spray device before use
- 1 nasal spray device contains 1 dose of medicine
- Each device sprays 1 time only
- Store at room temperature or refrigerated,
  between 2°C to 25°C (36°F to 77°F)
- Do not freeze
- Avoid excessive heat above 40°C (104°F)

Lot XXXXXX EXP YYYY-MMM

Distributed by Emergent Devices Inc.
Plymouth Meeting, PA 19462 USA A1160

Package/Label Principal Display Panel – Front and Back Label

NARCAN®
Naloxone HCl Nasal Spray 4 mg
141357
A1158

FOR USE IN THE NOSE ONLY
NDC 69547-627-02

A1159
Distributed by Emergent Devices, Inc.
Plymouth Meeting, PA 19462, USA
141358

Lot XXXXXX
EXP YYYY-MMM